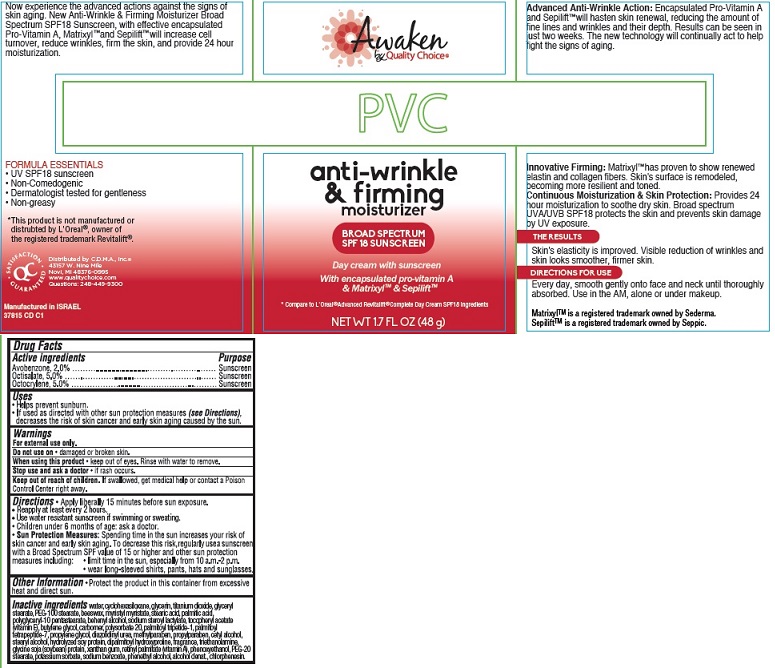 DRUG LABEL: Awaken by Quality Choice Anti-Wrinkle and Firming Moisturizer Day Broad Spectrum SPF18 Sunscreen
NDC: 63868-251 | Form: CREAM
Manufacturer: Chain Drug Marketing Association
Category: otc | Type: HUMAN OTC DRUG LABEL
Date: 20140930

ACTIVE INGREDIENTS: AVOBENZONE 2 g/100 g; OCTISALATE 5 g/100 g; OCTOCRYLENE 5 g/100 g
INACTIVE INGREDIENTS: WATER; CYCLOMETHICONE 6; GLYCERIN; TITANIUM DIOXIDE; GLYCERYL MONOSTEARATE; PEG-100 STEARATE; YELLOW WAX; MYRISTYL MYRISTATE; STEARIC ACID; PALMITIC ACID; POLYGLYCERYL-10 STEARATE; DOCOSANOL; SODIUM STEAROYL LACTYLATE; .ALPHA.-TOCOPHEROL ACETATE; BUTYLENE GLYCOL; POLYSORBATE 20; PALMITOYL TETRAPEPTIDE-7; PROPYLENE GLYCOL; DIAZOLIDINYL UREA; METHYLPARABEN; PROPYLPARABEN; CETYL ALCOHOL; STEARYL ALCOHOL; SOY PROTEIN; DIPALMITOYL HYDROXYPROLINE; TROLAMINE; XANTHAN GUM; VITAMIN A PALMITATE; PHENOXYETHANOL; PEG-20 STEARATE; POTASSIUM SORBATE; SODIUM BENZOATE; PHENYLETHYL ALCOHOL; ALCOHOL; CHLORPHENESIN

Awaken by Quality Choice®

Active ingredient

Avobenzone, 2.0%

Octisalate, 5.0%

Octocrylene, 5.0%

Purpose

Sunscreen

Uses

- Helps prevent sunburn.
- If used as directed with other sun protection measures (see Directions), decreases the risk of skin cancer and early skin aging caused by the sun.

Warnings

For external use only.

Do not use on

- damaged or broken skin.

When using this product

- keep out of eyes. Rinse with water to remove.

Stop use and ask a doctor

- if rash occurs.

Keep Out of Reach of Children.

If swallowed, get medical help or contact a Poison Control Center right away.

Directions

- Apply liberally 15 minutes before sun exposure.
- Reapply at least every 2 hours.
- Use water resistant sunscreen if swimming or sweating.
- Children under 6 months of age: ask a doctor.
- Sun Protection Measures: Spending time in the sun increases your risk of skin cancer and early skin aging. To decrease this risk, regularly use a sunscreen with a Broad Spectrum SPF value of 15 or higher and other sun protection measures including:
  1. limit time in the sun, especially from 10 a.m. – 2 p.m.
  2. wear long-sleeved shirts, pants, hats and sunglasses.

Other Information

- Protect the product in this container from excessive heat and direct sun.

Inactive ingredients

water, cyclohexasiloxane, glycerin, titanium dioxide, glyceryl stearate, PEG-100 stearate, beeswax, myristyl myristate, stearic acid, palmitic acid, polyglyceryl-10 pentastearate, behenyl alcohol, sodium steroyl lactylate, tocopheryl acetate (vitamin E), butylene glycol, carbomer, polysorbate 20, palmitoyl tripeptide-1, palmitoyl tetrapeptide-7, propylene glycol, diazolidinyl urea, methylparaben, propylparaben, cetyl alcohol, stearyl alcohol, hydrolyzed soy protein, dipalmitoyl hydroxyproline, fragrance, triethanolamine, glycine soja (soybean) protein, xanthan gum, retinyl palmitate (vitamin A), phenoxyethanol, PEG-20 stearate, potassium sorbate, sodium benzoate, phenethyl alcohol, alcohol denat., chlorphenesin.

Package/Label Principal Display Panel

Awaken
by Quality Choice®

anti-wrinkle
& firming
moisturizer

BROAD SPECTRUM
SPF 18 SUNSCREEN

Day cream with sunscreen

With encapsulated pro-vitamin A
& Matrixyl™ & Sepilift™

*Compare to L’Oreal® Advanced Revitalift® Complete Day Cream SPF18 ingredients

NET WT 1.7 FL OZ (48 g)

Advanced Anti-Wrinkle Action: Encapsulated Pro-Vitamin A and Sepilift™ will hasten skin renewal, reducing the amount of fine lines and wrinkles and their depth. Results can be seen in just two weeks. The new technology will continually act to help fight the signs of aging.

Innovative Firming: Matrixyl™ has proven to show renewed elastin and collagen fibers. Skin’s surface is remodeled, becoming more resilient and toned.

Continuous Moisturization & Skin Protection: Provides 24 hour moisturization to soothe dry skin. Broad spectrum UVA/UVB SPF18 protects the skin and prevents skin damage by UV exposure.

THE RESULTS

Skin’s elasticity is improved. Visible reduction of wrinkles and skin looks smoother, firmer skin.

DIRECTIONS FOR USE

Every day, smooth gently onto face and neck until thoroughly absorbed. Use in the AM, alone or under makeup.

Matrixyl™ is a registered trademark owned by Sederma.

Sepilift™ is a registered trademark owned by Seppic.

Now experience the advanced actions against the signs of skin aging. New Anti-Wrinkle & Firming Moisturizer Broad Spectrum SPF18 Sunscreen, with effective encapsulated Pro-Vitamin A, Matrixyl™ and Sepilift™ will increase cell turnover, reduce wrinkles, firm the skin, and provide 24 hour moisturization.

FORMULA ESSENTIALS

- UV SPF18 sunscreen
- Non-Comedogenic
- Dermatologist tested for gentleness
- Non-greasy

*This product is not manufactured or distrubted by L’Oreal®, owner of the registered trademark Revitalift®.

Distributed by C.D.M.A., Inc.©
43157 W. Nine Mile
Novi, MI 48376-0995
www.qualitychoice.com
Questions: 248-449-9300

SATISFACTION GUARANTEED

Manufactured in ISRAEL
37815 CD C1

Carton Label